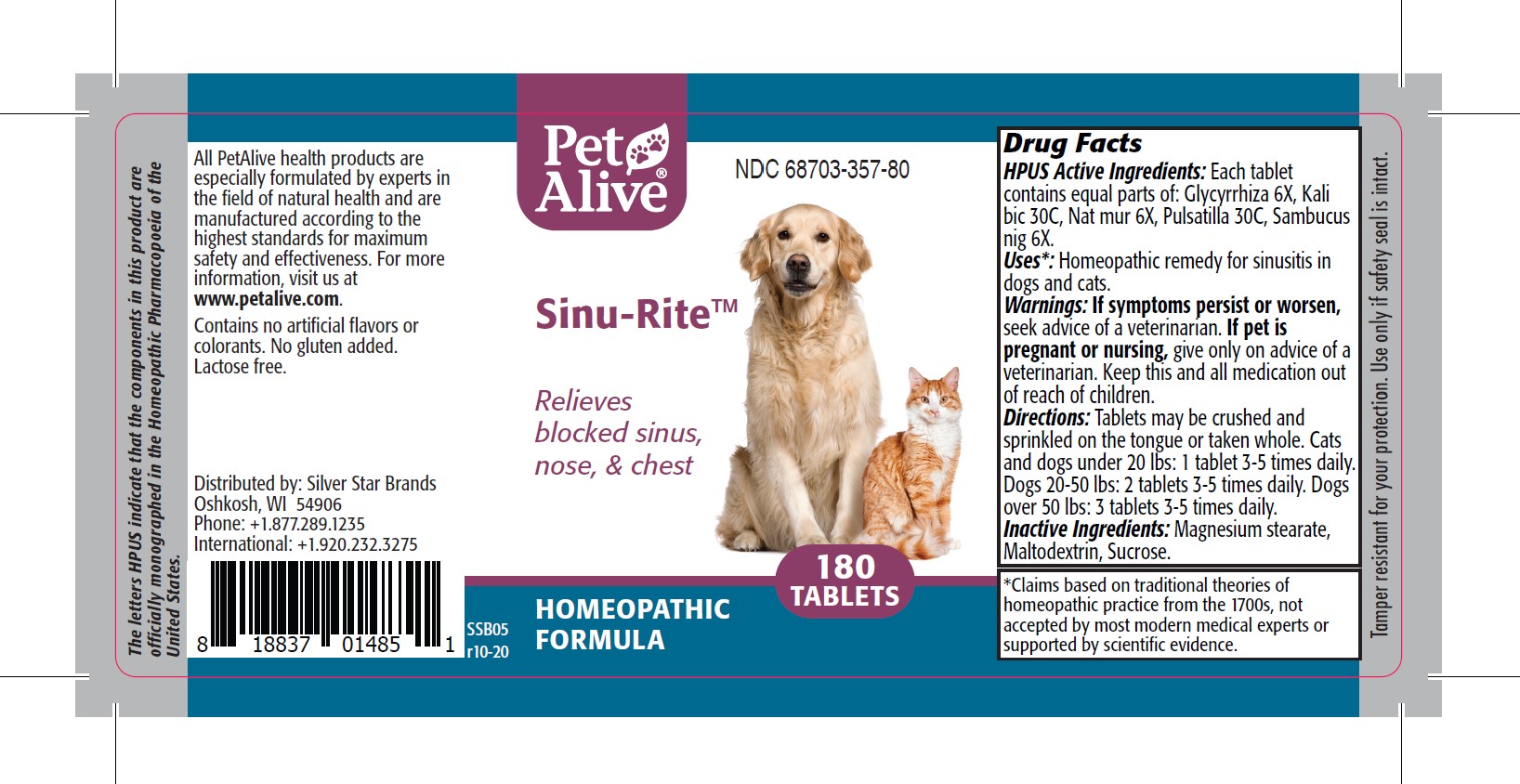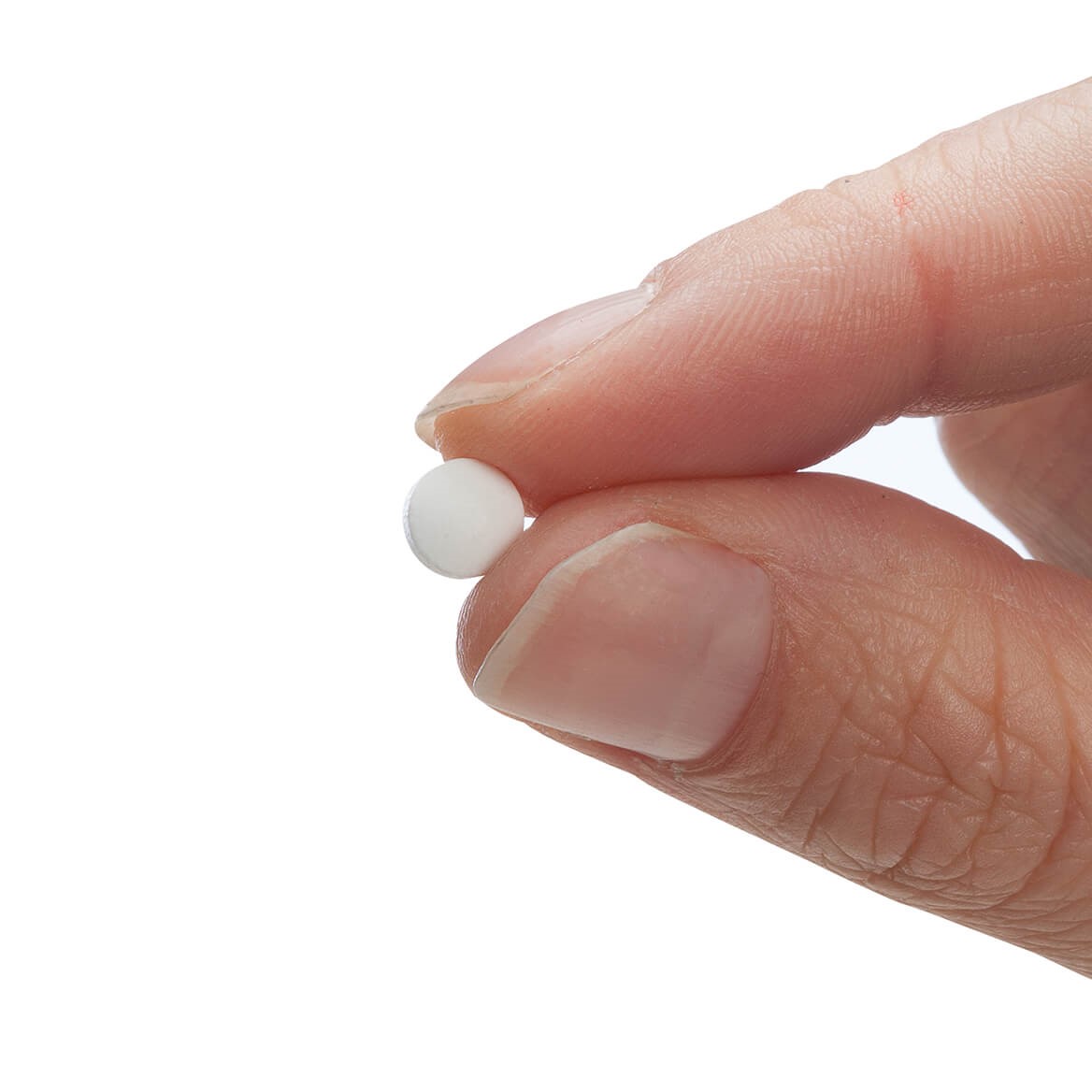 DRUG LABEL: Sinu-Rite
NDC: 68703-357 | Form: TABLET
Manufacturer: SILVER STAR BRANDS
Category: homeopathic | Type: HUMAN OTC DRUG LABEL
Date: 20251212

ACTIVE INGREDIENTS: GLYCYRRHIZA GLABRA 6 [hp_X]/180 1; SODIUM CHLORIDE 6 [hp_X]/180 1; POTASSIUM DICHROMATE 30 [hp_C]/180 1; SAMBUCUS NIGRA FLOWER 6 [hp_X]/180 1; PULSATILLA VULGARIS 30 [hp_C]/180 1
INACTIVE INGREDIENTS: MALTODEXTRIN; MAGNESIUM STEARATE; SUCROSE

PetAlive® Sinu-Rite™

HPUS Active Ingredients: Each tablet contains equal parts of: Glycyrrhiza 6X, Kali bic 30C, Nat mur 6X, Pulsatilla 30C, Sambucus nig 6X.

Uses*

Uses*: Homeopathic remedy for sinusitis in dogs and cats.

Warnings

Warnings: If symptoms persist or worsen, seek advice of a veterinarian. if pet is pregnant or nursing, give only on advice of a veterinarian. Keep this and all medication out of reach of children.

Directions

Directions: Tablets may be crushed and sprinkled on the tongue or taken whole. Cats and dogs under 20 lbs: 1 tablet 3-5 times daily. Dogs 20-50 lbs: 2 tablets 3-5 times daily. Dogs over 50 lbs: 3 tablets 3-5 times daily.

OTHER SAFETY INFORMATION

Tamper resistant for your protection. Use only if safety seal is intact.

Contains no artificial flavors or colorants. No gluten added. Lactose free.

Inactive Ingredients:

Inactive Ingredients: Magnesium Stearate, Maltodextrin, Sucrose.

KEEP OUT OF REACH OF CHILDREN

Keep this and all medication out of reach of children.

PREGNANCY OR BREAST FEEDING

If pet is pregnant or nursing, give only on advice of a veterinarian.

PURPOSE

Relieves blocked sinus, nose, & chest